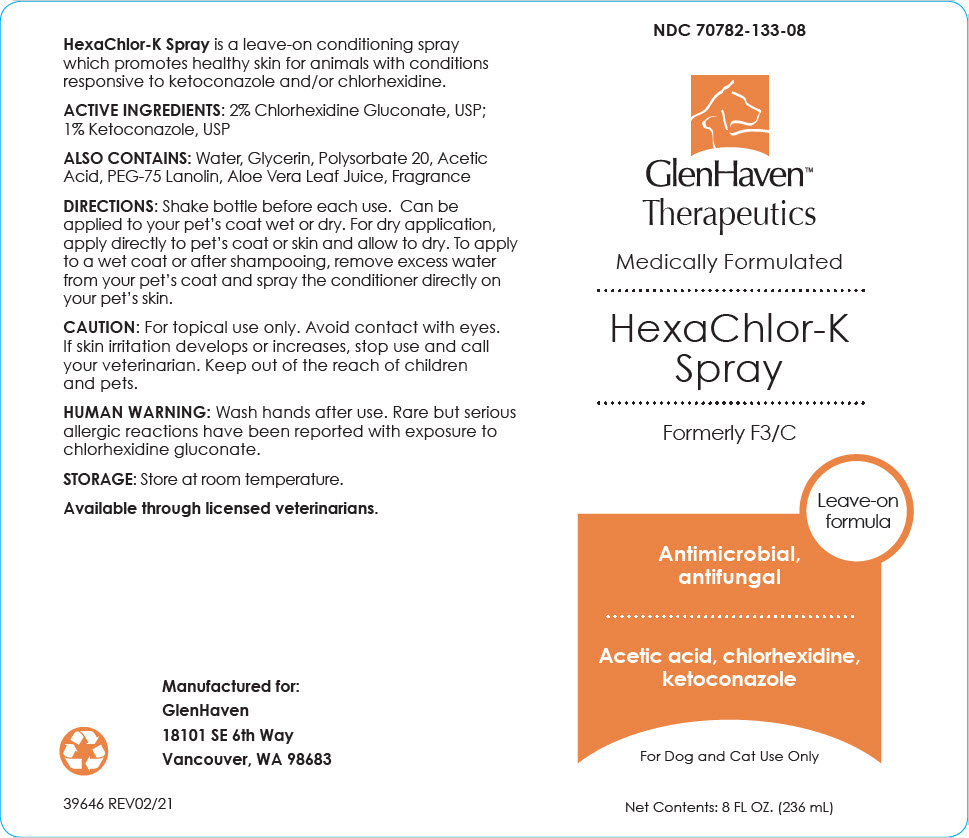 DRUG LABEL: HexaChlor-K
NDC: 70782-133 | Form: SPRAY
Manufacturer: GlenHaven LLC
Category: animal | Type: OTC ANIMAL DRUG LABEL
Date: 20210811

ACTIVE INGREDIENTS: CHLORHEXIDINE GLUCONATE 20 mg/1 mL; KETOCONAZOLE 10 mg/1 mL

HexaChlor-K Spray

VETERINARY INDICATIONS

HexaChlor-K Spray is a leave-on conditioning spray which promotes healthy skin for animals with conditions responsive to ketoconazole and/or chlorhexidine.

DESCRIPTION

ACTIVE INGREDIENTS: 2% Chlorhexidine Gluconate, USP; 1% Ketoconazole, USP

ALSO CONTAINS: Water, Glycerin, Polysorbate 20, Acetic Acid, PEG-75 Lanolin, Aloe Vera Leaf Juice, Fragrance

DOSAGE AND ADMINISTRATION

DIRECTIONS: Shake bottle before each use. Can be applied to your pet's coat wet or dry. For dry application, apply directly to pet's coat or skin and allow to dry. To apply to a wet coat or after shampooing, remove excess water from your pet's coat and spray the conditioner directly on your pet's skin.

PRECAUTIONS

CAUTION: For topical use only. Avoid contact with eyes. If skin irritation develops or increases, stop use and call your veterinarian. Keep out of the reach of children and pets.

SAFE HANDLING WARNING

HUMAN WARNING: Wash hands after use. Rare but serious allergic reactions have been reported with exposure to chlorhexidine gluconate.

STORAGE: Store at room temperature.

Available through licensed veterinarians.

Manufactured for:
GlenHaven
18101 SE 6th Way
Vancouver, WA 98683

39646 REV02/21

PRINCIPAL DISPLAY PANEL - 236 mL Bottle Label

NDC 70782-133-08

GlenHaven™
Therapeutics

Medically Formulated

HexaChlor-K
Spray

Formerly F3/C

Leave-on
formula

Antimicrobial,
antifungal

Acetic acid, chlorhexidine,
ketoconazole

For Dog and Cat Use Only

Net Contents: 8 FL OZ. (236 mL)